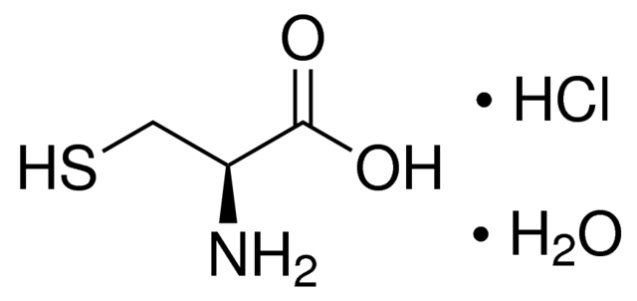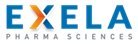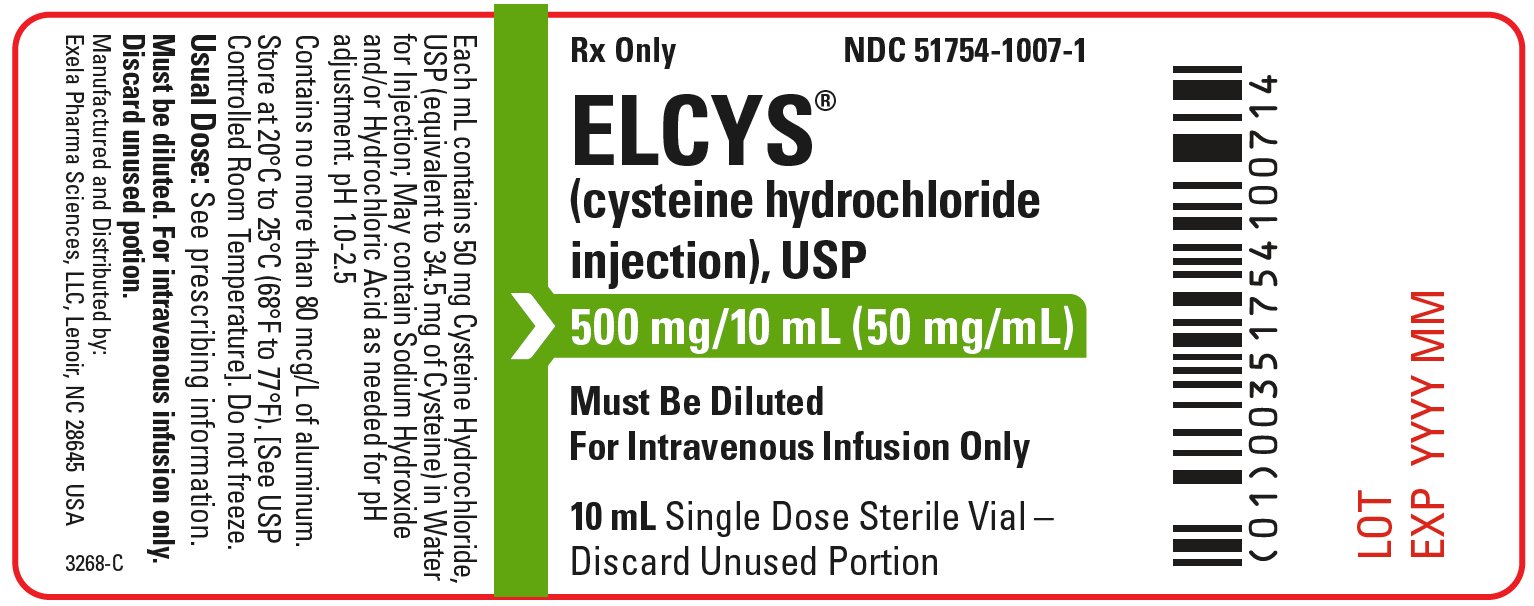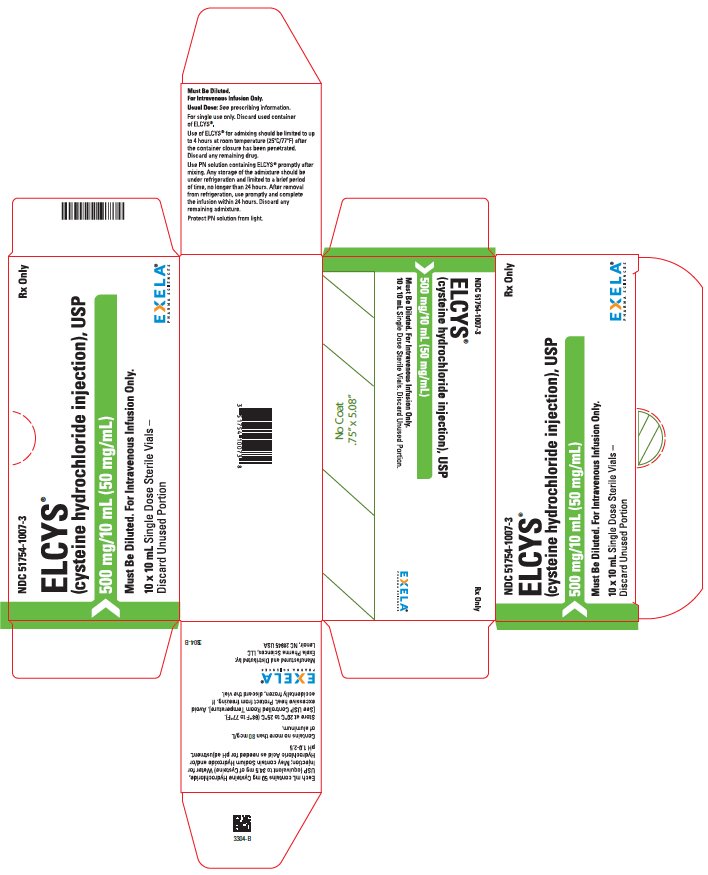 DRUG LABEL: ELCYS
NDC: 51754-1007 | Form: INJECTION, SOLUTION
Manufacturer: Exela Pharma Sciences, LLC
Category: prescription | Type: HUMAN PRESCRIPTION DRUG LABEL
Date: 20240201

ACTIVE INGREDIENTS: CYSTEINE HYDROCHLORIDE 10 mg/1 mL

HIGHLIGHTS OF PRESCRIBING INFORMATION

These highlights do not include all the information needed to use ELCYS safely and effectively. See full prescribing information for ELCYS.
Initial U.S. Approval: 1971

1 INDICATIONS AND USAGE

ELCYS is a sulfur-containing amino acid indicated to meet the nutritional requirements of newborn infants requiring total parenteral nutrition (TPN); and of adult and pediatric patients with severe liver disease who may have impaired enzymatic processes and require TPN. It can also be added to amino acid solutions to provide a more complete profile of amino acids for protein synthesis. (1)

2 DOSAGE AND ADMINISTRATION

- ELCYS is for admixing use only. Not for direct intravenous infusion. (2.1)
- See full prescribing information for information on preparation, administration, instructions for use, dosing considerations, including the recommended dosage in pediatric patients and adults. (2.1, 2.2, 2.3, 2.4, 2.5)

3 DOSAGE FORMS AND STRENGTHS

Injection: 500 mg/10 mL (50 mg/mL) cysteine hydrochloride, USP in a 10 mL single-dose vial. (3)

4 CONTRAINDICATIONS

- Hypersensitivity to one or more amino acids (4)
- Inborn errors of amino acid metabolism (4)
- Pulmonary edema or acidosis due to low cardiac output (4)

5 WARNINGS AND PRECAUTIONS

- Pulmonary Embolism due to Pulmonary Vascular Precipitates: If signs of pulmonary distress occur, stop the infusion and initiate a medical evaluation. (5.1)
- Vein Damage and Thrombosis: Solutions with osmolarity of 900 mOsm/L or more must be infused through a central catheter. (2.1, 5.2)
- Increased blood urea nitrogen (BUN): Monitor laboratory parameters and discontinue if exceeds normal postprandial limits and continues to increase. (5.3)
- Acid-Base Imbalance: Monitor laboratory parameters and supplement with electrolytes as needed. (5.4)
- Hepatobiliary Disorders: Monitor liver function parameters and ammonia levels. (5.5)
- Hyperammonemia: Neurocognitive delay possible in infants; monitor blood ammonia levels. (5.6, 8.4)
- Aluminium Toxicity: Increased risk in patients with renal impairment, including preterm infants. (5.7, 8.4)
- Monitoring and Laboratory Tests: Monitor fluid and electrolytes, serum osmolarity, blood glucose, kidney and liver function, blood count and coagulation parameters throughout treatment. (5.8)

6 ADVERSE REACTIONS

Most common adverse reactions are local reactions (warm sensation, erythema, phlebitis and thrombosis at the infusion site), generalized flushing, fever and nausea (6).

To report SUSPECTED ADVERSE REACTIONS, contact Exela Pharma Sciences, LLC or FDA at 1-800-FDA-1088 or www.fda.gov/medwatch.

FULL PRESCRIBING INFORMATION

1 INDICATIONS AND USAGE

ELCYS is indicated for use as an additive to amino acid solutions to meet the nutritional requirements of newborn infants

requiring total parenteral nutrition (TPN) and of adult and pediatric patients with severe liver disease who may have

impaired enzymatic processes and require TPN. It can also be added to amino acid solutions to provide a more complete

profile of amino acids for protein synthesis.

2 DOSAGE AND ADMINISTRATION

2.1 Important Administration Information

ELCYS is for admixing use only. It is not for direct intravenous infusion. Prior to administration, ELCYS must be diluted

and used as an admixture in parenteral nutrition (PN) solutions.

The resulting solution is for intravenous infusion into a central or peripheral vein. The choice of a central or peripheral

venous route should depend on the osmolarity of the final infusate. Solutions with osmolarity of 900 mOsm/L or greater

must be infused through a central catheter [see Warnings and Precautions (5.2)].

2.2 Preparation and Administration Instructions

- ELCYS is not for direct intravenous infusion. Prior to administration, ELCYS must be diluted and used as anadmixture in PN solutions.
- ELCYS is to be prepared only in a suitable work area such as a laminar flow hood (or an equivalent clean air compounding area). The key factor in the preparation is careful aseptic technique to avoid inadvertent touch contamination during mixing of solutions and addition of other nutrients.
- ELCYS is for addition to amino acid solutions prior to further admixing with dextrose injection using a PN container.
- Use a dedicated line for PN solutions.
- Intravenous lipid emulsions can be infused concurrently into the same vein as ELCYS containing amino acid and dextrose solutions by a Y-connector located near the infusion site; flow rates of each solution should be controlled separately by infusion pumps.
- For administration without lipid emulsion, use a 0.22 micron in-line filter.
- To prevent air embolism, use a non-vented infusion set or close the vent on a vented set, avoid multiple connections, do not connect flexible containers in series, fully evacuate residual gas in the container prior to administration, do not pressurize the flexible container to increase flow rates, and if administration is controlled by a pumping device, turn off pump before the container runs dry.
- If infused with lipid emulsion, do not use administration sets and lines that contain di-2-ethylhexyl phthalate (DEHP). Administration sets that contain polyvinyl chloride (PVC) components have DEHP as a plasticizer.
- Visually inspect the diluted PN solution containing ELCYS for particulate matter before admixing, after admixing, and prior to administration. The solution should be clear and there should be no precipitates. A slight yellow color does not alter the quality and efficacy of this product.

2.3 Preparation Instructions for Admixing Using a Parenteral Nutrition (PN) Container

- Remove ELCYS vial from the carton and inspect for particulate matter.
- Transfer the required amount of ELCYS to an amino acid solution using strict aseptic techniques to avoid microbial contamination.
- The amino acid solution containing ELCYS can then be used to prepare admixtures in the PN container using strict aseptic techniques.
- Amino acids solution containing ELCYS may be mixed with dextrose injection. The following proper mixing sequence must be followed to minimize pH related problems:
- Transfer dextrose injection to the parental nutrition pooling container
- Transfer phosphate salt
- Transfer ELCYS-containing amino acid solution
- Transfer electrolytes
- Transfer trace elements
- Use gentle agitation during admixing to minimize localized concentration effects; shake containers gently after each addition.
- For automated compounding, refer to Instructions for Use of the applicable compounder.
- Because additives may be incompatible, evaluate all additions to the PN container for compatibility and stability of the resulting preparation. Consult with pharmacist, if available. Questions about compatibility may be directed to Exela Pharma Sciences, LLC. If it is deemed advisable to introduce additives to the PN container, use aseptic technique.
- Inspect the final PN solution containing ELCYS to ensure that precipitates have not formed during mixing or addition on additives. Discard if any precipitates are observed.

Stability and Storage

- For single use only. Discard used container of ELCYS.
- Use of ELCYS for admixing should be limited to up to 4 hours at room temperature (25ºC/77ºF) after the container closure has been penetrated. Discard any remaining drug.
- Use PN solution containing ELCYS promptly after mixing. Any storage of the admixture should be under refrigeration and limited to a brief period of time, no longer than 24 hours. After removal from refrigeration, use promptly and complete the infusion within 24 hours. Discard any remaining admixture.
- Protect PN solution from light.

2.4 Dosing Considerations

- The dosage of the final PN solution containing ELCYS must be based on the concentrations of all components in the solution and the recommended nutritional requirements [see Dosage and Administration (2.5)]. Consult the prescribing information of all added components to determine the recommended nutritional requirements for dextrose and lipid emulsion, as applicable.
- The dosage of ELCYS should be individualized based on the patient’s clinical condition (ability to adequately metabolize amino acids), body weight and nutritional/fluid requirements, as well as additional energy given orally/enterally to the patient. Prior to initiating parenteral nutrition, the following patient information should be reviewed: review of all medications, gastrointestinal function and laboratory data (such as electrolytes (including magnesium, calcium, and phosphorus), glucose, urea/creatinine, liver panel, complete blood count and triglyceride level (if adding lipid emulsion).
- Prior to administration of PN solution containing ELCYS, correct severe fluid, electrolyte and acid-base disorders.

2.5 Recommended Dosage in Pediatric Patients and Adults

The recommended dosage and volume of ELCYS is shown in Table 1 and is based upon the recommended daily protein

(amino acids) requirement. For pediatric patients from birth to less than 12 years of age, the recommended dosage of

ELCYS is 22 mg/gram of amino acids. For adults and pediatric patients 12 years of age and older, the recommended

dosage of ELCYS is 7 mg/gram of amino acids.

Table 1. Recommended Daily Dosage of ELCYS in Pediatric Patients and Adults

Age | Recommended Proteina Requirement (g AA/kg/day)1 | Recommended Dosage (mg ELCYS/g AA) | Recommended Volume (mL ELCYS/g AA)
Preterm and term infants less than 1 month of age | 3 to 4 | 22 | 0.44
Pediatric patients 1 month to less than 1 year of age | 2 to 3 | 22 | 0.44
Pediatric patients 1 year to 11 years of age | 1 to 2 | 22 | 0.44
Pediatric patients 12 years to 17 years of age | 0.8 to 1.5 | 7 | 0.14
Adults: Stable Patients | 0.8 to 1 | 7 | 0.14
Adults: Critically Ill Patientsb | 1.5 to 2 | 7 | 0.14

AA = Amino Acid

a Protein is provided as amino acids (AA).

b Includes patients requiring more than 2 to 3 days in the intensive care unit with organ failure, sepsis or postoperative major surgery. Do not use in patients with

conditions that are contraindicated [see Contraindications (4)]

ELCYS contains 50 mg/mL of cysteine hydrochloride (equivalent to 34.5 mg/mL of cysteine). Therefore, the ELCYS

dosages in Table 1 provide:

- 15 mg cysteine/gram of amino acids for pediatric patients less than 12 years of age
- 5 mg cysteine/gram of amino acids for adults and pediatric patients 12 years of age and older

3 DOSAGE FORMS AND STRENGTHS

Injection: 500 mg/10 mL (50 mg/mL) cysteine hydrochloride, USP as a clear, colorless, sterile solution in a 10 mL single-dose vial.

4 CONTRAINDICATIONS

ELCYS is contraindicated in:

- Patients with known hypersensitivity to one or more amino acids.
- Patients with inborn errors of amino acid metabolism due to risk of severe metabolic or neurologic complications.
- Patients with pulmonary edema or acidosis due to low cardiac output.

5 WARNINGS AND PRECAUTIONS

5.1 Pulmonary Embolism due to Pulmonary Vascular Precipitates

Pulmonary vascular precipitates causing pulmonary vascular emboli and pulmonary distress have been reported in

patients receiving PN. In some fatal cases, pulmonary embolism occurred as a result of calcium phosphate precipitates.

Precipitation following passage through an in-line filter and suspected in vivo precipitate formation has also been

reported. If signs of pulmonary distress occur, stop the PN infusion and initiate a medical evaluation. In addition to

inspection of the solution [see Dosage and Administration (2.1, 2.2)], the infusion set and catheter should also

periodically be checked for precipitates.

5.2 Vein Damage and Thrombosis

ELCYS must be diluted and used as an admixture in PN solutions. It is not for direct intravenous infusion. Solutions with

an osmolarity of 900 mOsm/L or greater must be infused through a central catheter [see Dosage and Administration

(2.1)]. The infusion of hypertonic nutrient injections into a peripheral vein may result in vein irritation, vein damage,

and/or thrombosis. The primary complication of peripheral access is venous thrombophlebitis, which manifests as pain,

erythema, tenderness or a palpable cord. Remove the catheter as soon as possible, if thrombophlebitis develops.

5.3 Increased Blood Urea Nitrogen (BUN)

Intravenous infusion of amino acids may induce a rise in blood urea nitrogen (BUN), especially in patients with impaired

hepatic or renal function. Appropriate laboratory tests should be performed periodically and infusion discontinued if BUN

levels exceed normal postprandial limits and continue to rise. It should be noted that a modest rise in BUN normally

occurs as a result of increased protein intake.

Administration of amino acid solutions in the presence of impaired renal function may augment an increasing BUN, as

does any protein dietary component.

5.4 Acid-Base Imbalance

Administration of ELCYS may result in metabolic acidosis in preterm infants.

Administration of amino acid solutions to a patient with hepatic impairment may result in serum amino acid imbalances,

metabolic alkalosis, prerenal azotemia, hyperammonemia, stupor and coma.

Frequent clinical evaluation and laboratory determinations are necessary for proper monitoring of acid-base balance

during parenteral nutrition therapy. Significant deviations from normal concentrations may require the use of additional

electrolyte supplements.

5.5 Hepatobiliary Disorders

Hepatobiliary disorders are known to develop in some patients without preexisting liver disease who receive PN,

including cholecystitis, cholelithiasis, cholestasis, hepatic steatosis, fibrosis and cirrhosis, possibly leading to hepatic

failure. The etiology of these disorders is thought to be multifactorial and may differ between patients.

Monitor liver function parameters and ammonia levels. Patients developing signs of hepatobiliary disorders should be

assessed early by a clinician knowledgeable in liver diseases in order to identify possible causative and contributory

factors, and possible therapeutic and prophylactic interventions.

5.6 Hyperammonemia

Hyperammonemia is of special significance in infants, as it can result in neurocognitive delays. Therefore, it is essential

that blood ammonia levels be measured frequently in infants.

Instances of asymptomatic hyperammonemia have been reported in patients without overt liver dysfunction. The

mechanisms of this reaction are not clearly defined but may involve genetic defects and immature or subclinically

impaired liver function [see Contraindications (4), Use in Specific Populations (8.4)].

5.7 Aluminum Toxicity

ELCYS contains aluminum that may be toxic.

Aluminum may reach toxic levels with prolonged parenteral administration in patients with renal impairment. Preterm

infants are particularly at risk for aluminum toxicity because their kidneys are immature, and they require large amounts

of calcium and phosphate solutions, which also contain aluminum.

Patients with renal impairment, including preterm infants, who receive greater than 4 to 5 mcg/kg/day of parenteral

aluminum can accumulate aluminum to levels associated with central nervous system and bone toxicity. Tissue loading

may occur at even lower rates of administration.

Exposure to aluminum from ELCYS is not more than 0.21 mcg/kg/day when preterm and term infants less than 1 month

of age are administered the recommended maximum dosage of ELCYS (15 mg cysteine/g of amino acids and 4 g of

amino acids/kg/day) [see Table 1, Dosage and Administration (2.5)]. When prescribing ELCYS for use in PN containing

other small volume parenteral products, the total daily patient exposure to aluminum from the admixture should be

considered and maintained at no more than 5 mcg/kg/day [see Use in Specific Populations (8.4)].

5.8 Monitoring and Laboratory Tests

Monitor fluid and electrolyte status, serum osmolarity, blood glucose, liver and kidney function, blood count and

coagulation parameters throughout treatment [see Dosage and Administration (2.4)].

6 ADVERSE REACTIONS

The following serious adverse reactions are discussed in greater detail in other sections of the prescribing information:

- Pulmonary embolism due to pulmonary vascular precipitates [see Warnings and Precautions (5.1)]
- Vein damage and thrombosis [see Warnings and Precautions (5.2)]
- Increased BUN [see Warnings and Precautions (5.3)]
- Acid-base imbalance [see Warnings and Precautions (5.4)]
- Hepatobiliary disorders [see Warnings and Precautions (5.5)]
- Hyperammonemia [see Warnings and Precautions (5.6)]
- Aluminum toxicity [see Warnings and Precautions (5.7)]

Adverse reactions with the use of cysteine hydrochloride injection were identified in clinical studies or postmarketing reports. Because some of these reactions were reported voluntarily from a population of uncertain size, it is not always possible to reliably estimate their frequency or establish a causal relationship to drug exposure.

- Local infusion site reactions, including a warm sensation, erythema, phlebitis and thrombosis at the infusion site
- Generalized flushing, fever and nausea

8 USE IN SPECIFIC POPULATIONS

8.1 Pregnancy

Risk Summary

Appropriate administration of ELCYS is not expected to cause major birth defects, miscarriage or adverse maternal or

fetal outcomes. Animal reproduction studies have not been conducted with cysteine hydrochloride.

The estimated background risk for major birth defects and miscarriage for the indicated populations is unknown. All

pregnancies have a background risk of birth defect, loss or other adverse outcomes. In the U.S. general population, the

estimated background risk of major birth defect and miscarriage in the clinically recognized pregnancies is 2 to 4% and 15

to 20%, respectively.

8.2 Lactation

Risk Summary

Data available on the effects of cysteine hydrochloride on infants, either directly or through breastmilk, do not suggest a

significant risk of adverse events from exposure. Although there are no data on the presence of cysteine hydrochloride in

human or animal milk or the effects on milk production, appropriate administration of ELCYS is not expected to cause

harm to a breastfed infant. The development and health benefits of breastfeeding should be considered along with the

mother’s clinical need for ELCYS and any potential adverse effects on the breastfed infant from ELCYS or from the

underlying maternal condition.

8.4 Pediatric Use

ELCYS is approved for use in pediatric patients, from birth to 17 years of age, for use as an additive to amino acid

solutions to meet the nutritional requirements of newborn infants, including preterm infants, requiring total parenteral

nutrition (TPN) and pediatric patients with severe liver disease who may have impaired enzymatic processes and require

TPN. The safety profile for ELCYS use in pediatric patients includes risks of acid-base imbalance and hyperammonemia.

Acid-base imbalance, including metabolic acidosis, may occur with ELCYS administration in preterm infants. Frequent

clinical and laboratory assessments are necessary to monitor and manage fluid balance, electrolyte concentrations, and

acid-base balance during parenteral nutrition therapy [see Warnings and Precautions (5.4)].

Hyperammonemia is of special significance in infants (birth to two years of age). This reaction appears to be related to a

deficiency of the urea cycle amino acids of genetic or product origin. It is essential that blood ammonia be measured

frequently in infants [see Warnings and Precautions (5.6)].

Because of immature renal function, preterm infants receiving prolonged PN treatment with ELCYS may be at higher risk

of aluminum toxicity [see Warnings and Precautions (5.7)].

8.5 Geriatric Use

Clinical studies with ELCYS have not been performed to determine whether patients aged 65 and over respond differently

from younger patients.

8.6 Renal Impairment

Monitor patients with impaired renal function receiving PN solutions containing the recommended dosage of ELCYS with

frequent clinical evaluation and laboratory tests to assess renal function, including serum electrolytes and fluid balance

[see Dosage and Administration (2.4), Warnings and Precautions (5.8)].

8.7 Hepatic Impairment

Monitor patients with impaired liver function receiving PN solutions containing the recommended dosage of ELCYS with

frequent clinical evaluation and laboratory tests to assess liver function, such as bilirubin and liver function parameters

[see Dosage and Administration (2.4), Warnings and Precautions (5.8)].

10 OVERDOSAGE

In the event of over hydration or solute overload, re-evaluate the patient and institute appropriate corrective measures [see

Warnings and Precautions (5.3, 5.4, 5.5, 5.7, 5.8)].

11 DESCRIPTION

ELCYS (cysteine hydrochloride injection) is a sterile, nonpyrogenic solution for intravenous use. Each 10 mL of ELCYS

contains 500 mg of cysteine hydrochloride, USP (equivalent to 345 mg of cysteine) in water for injection. Sodium

hydroxide and/or hydrochloric acid are used as needed to adjust the pH. The pH range is 1.0 to 2.5.

The active ingredient is cysteine hydrochloride. Cysteine is a sulfur-containing amino acid. The chemical name of

cysteine hydrochloride is L-cysteine hydrochloride monohydrate and is chemically designated as C3H7NO2S • HCI • H2O

having a molecular weight of 175.63. Cysteine hydrochloride is a white crystalline powder soluble in water. Cysteine

aqueous solution is prone to oxidation when exposed to air, and when mixed with amino acids solutions, cysteine may

convert to insoluble cystine which leads to precipitation over time. It has the following structural formula:

ELCYS contains no more than 80 mcg/L of aluminum.

12 CLINICAL PHARMACOLOGY

12.1 Mechanism of Action

Endogenous cysteine is synthesized from methionine by the enzyme, cystathionase, via the trans-sulfuration pathway, and

serves as a precursor substrate for both glutathione and taurine. ELCYS provides cysteine to the systemic circulation of

patients who require PN and cannot synthesize adequate quantities of cysteine due to insufficient or deficient

cystathionase activity.

15 REFERENCES

1. Ayers P. et al. A.S.P.E.N. Parenteral Nutrition Handbook, 2nd ed. 2014 pg. 123 and 124.

16 HOW SUPPLIED/STORAGE AND HANDLING

ELCYS is supplied as follows:

500 mg/10 mL (50 mg/mL) of cysteine hydrochloride, USP is a clear, colorless, sterile and nonpyrogenic solution in 10

mL single-dose vials (51754-1007-1), packaged as 10 per carton (NDC 51754-1007-3)

Store at 20°C to 25°C (68°F to 77°F). [See USP Controlled Room Temperature]. Avoid excessive heat. Protect from

freezing. If accidentally frozen, discard the vial.

For storage of admixed solution see Dosage and Administration (2.3).

17 PATIENT COUNSELING INFORMATION

Inform patients, caregivers, or home healthcare providers of the following risks of ELCYS:

- Pulmonary embolism due to pulmonary vascular precipitates [see Warnings and Precautions (5.1)]
- Vein damage and thrombosis [see Warnings and Precautions (5.2)]
- Increased BUN [see Warnings and Precautions (5.3)]
- Acid base imbalance [see Warnings and Precautions (5.4)]
- Hepatobiliary disorders [see Warnings and Precautions (5.5)]
- Hyperammonemia [see Warnings and Precautions (5.6)]
- Aluminum toxicity [see Warnings and Precautions (5.7)]
- Monitoring and laboratory tests [see Warnings and Precautions (5.8)]

Manufactured and Distributed by:

Exela Pharma Sciences, LLC

Lenoir, NC 28645

PACKAGE/LABEL PRINCIPAL DISPLAY PANEL-Vial Label

Rx Only NDC 51754-1007-1

ELCYS

(Cysteine Hydrochloride

Injection), USP

500 mg/10 mL (50 mg/mL)

Must Be Diluted

For Intravenous Use Only After Dilution

10 mL Single Dose Sterile Vial-

Discard Unused Portion

PACKAGE/LABEL PRINCIPAL DISPLAY PANEL-Carton Label

NDC 51754-1007-3 Rx Only

ELCYS

(Cysteine Hydrochloride Injection), USP

500 mg/10 mL (50 mg/mL)

Must Be Diluted. For Intravenous Use Only.

10 x 10 mL Single Dose SterileVials-

Discard Unused Portion